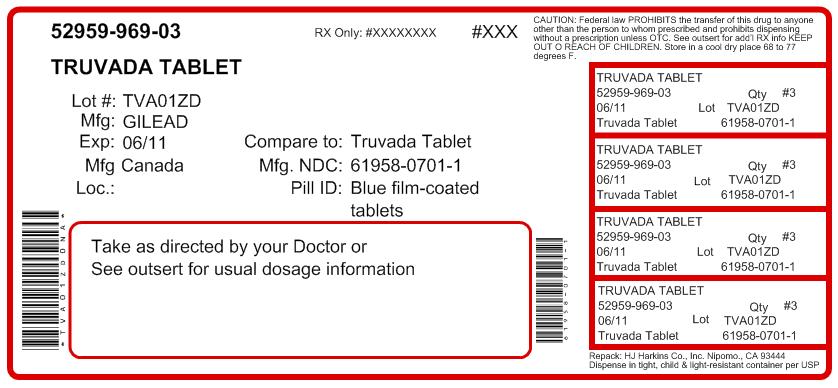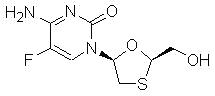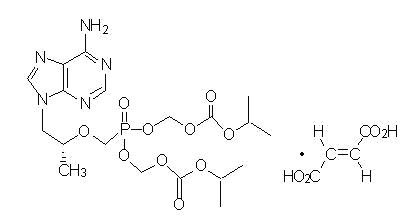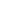 DRUG LABEL: Truvada
NDC: 52959-969 | Form: TABLET, FILM COATED
Manufacturer: H.J. Harkins Company, Inc.
Category: prescription | Type: HUMAN PRESCRIPTION DRUG LABEL
Date: 20111214

ACTIVE INGREDIENTS: emtricitabine 200 mg/1 1; tenofovir disoproxil fumarate 300 mg/1 1
INACTIVE INGREDIENTS: croscarmellose sodium; lactose monohydrate; magnesium stearate; cellulose, microcrystalline; starch, corn; water; FD&C Blue No. 2; aluminum oxide; hypromelloses; titanium dioxide; triacetin

HIGHLIGHTS OF PRESCRIBING INFORMATION

These highlights do not include all the information needed to use TRUVADA safely and effectively. See full prescribing information for TRUVADA.
TRUVADA® (emtricitabine/tenofovir disoproxil fumarate) tablets
Initial U.S. Approval: 2004

WARNINGS: LACTIC ACIDOSIS/SEVERE HEPATOMEGALY WITH STEATOSIS and POST TREATMENT ACUTE EXACERBATION OF HEPATITIS B

See full prescribing information for complete boxed warning.

- Lactic acidosis and severe hepatomegaly with steatosis, including fatal cases, have been reported with the use of nucleoside analogs, including VIREAD, a component of TRUVADA. (5.1)
- TRUVADA is not approved for the treatment of chronic hepatitis B virus (HBV) infection. Severe acute exacerbations of hepatitis B have been reported in patients coinfected with HIV-1 and HBV who have discontinued TRUVADA. Hepatic function should be monitored closely in these patients. If appropriate, initiation of anti-hepatitis B therapy may be warranted. (5.2)

RECENT MAJOR CHANGES

Indications and Usage (1) | 7/2011
Dosage and Administration (2.1, 2.2) | 7/2011
Warnings and Precautions
Decreases in Bone Mineral Density (5.5) | 7/2011

1 INDICATIONS AND USAGE

TRUVADA, a combination of EMTRIVA and VIREAD, both nucleoside analog HIV-1 reverse transcriptase inhibitors, is indicated in combination with other antiretroviral agents for the treatment of HIV-1 infection in adults and pediatric patients 12 years of age and older. (1)

2 DOSAGE AND ADMINISTRATION

- Recommended dose in adults and pediatric patients (12 years of age and older and weighing greater than or equal to 35 kg): One tablet (containing 200 mg of emtricitabine and 300 mg of tenofovir disoproxil fumarate) once daily taken orally with or without food. (2.1)
- Dose recommended in renal impairment:
  Creatinine clearance 30–49 mL/min: 1 tablet every 48 hours. (2.2)
  CrCl below 30 mL/min or hemodialysis: Do not use TRUVADA. (2.2)

3 DOSAGE FORMS AND STRENGTHS

Tablets: 200 mg of emtricitabine and 300 mg of tenofovir disoproxil fumarate. (3)

4 CONTRAINDICATIONS

None. (4)

5 WARNINGS AND PRECAUTIONS

- New onset or worsening renal impairment: Can include acute renal failure and Fanconi syndrome. Assess creatinine clearance (CrCl) before initiating treatment with TRUVADA. Monitor CrCl and serum phosphorus in patients at risk. Avoid administering Truvada with concurrent or recent use of nephrotoxic drugs. (5.3)
- Coadministration with Other Products: Do not use with drugs containing emtricitabine or tenofovir disoproxil fumarate including ATRIPLA, EMTRIVA, VIREAD; or with drugs containing lamivudine. Do not administer in combination with HEPSERA. (5.4)
- Decreases in bone mineral density (BMD): Consider assessment of BMD in patients with a history of pathologic fracture or other risk factors for osteoporosis or bone loss. (5.5)
- Redistribution/accumulation of body fat: Observed in patients receiving antiretroviral therapy. (5.6)
- Immune reconstitution syndrome: May necessitate further evaluation and treatment. (5.7)
- Triple nucleoside-only regimens: Early virologic failure has been reported in HIV-infected patients. Monitor carefully and consider treatment modification. (5.8)

6 ADVERSE REACTIONS

Most common adverse reactions (incidence greater than or equal to 10%) are diarrhea, nausea, fatigue, headache, dizziness, depression, insomnia, abnormal dreams, and rash. (6)

To report SUSPECTED ADVERSE REACTIONS, contact Gilead Sciences, Inc. at 1-800-GILEAD-5 or FDA at 1-800-FDA-1088 or www.fda.gov/medwatch

7 DRUG INTERACTIONS

- Didanosine: Tenofovir disoproxil fumarate increases didanosine concentrations. Use with caution and monitor for evidence of didanosine toxicity (e.g., pancreatitis, neuropathy) when coadministered. Consider dose reductions or discontinuations of didanosine if warranted. (7.1)
- Atazanavir: Coadministration decreases atazanavir concentrations and increases tenofovir concentrations. Use atazanavir with TRUVADA only with ritonavir; monitor for evidence of tenofovir toxicity. (7.2)
- Lopinavir/ritonavir: Coadministration increases tenofovir concentrations. Monitor for evidence of tenofovir toxicity. (7.2)

8 USE IN SPECIFIC POPULATIONS

- Pregnancy: pregnancy registry available: Enroll patients by calling 1-800-258-4263.
- Nursing mothers: Women infected with HIV should be instructed not to breast feed. (8.3)
- Pediatrics: Safety and efficacy not established in patients less than 12 years of age. (8.4)

FULL PRESCRIBING INFORMATION

WARNINGS: LACTIC ACIDOSIS/SEVERE HEPATOMEGALY WITH STEATOSIS and POST TREATMENT ACUTE EXACERBATION OF HEPATITIS B

Lactic acidosis and severe hepatomegaly with steatosis, including fatal cases, have been reported with the use of nucleoside analogs, including VIREAD, a component of TRUVADA, in combination with other antiretrovirals [See Warnings and Precautions (5.1)].

TRUVADA is not approved for the treatment of chronic hepatitis B virus (HBV) infection and the safety and efficacy of TRUVADA have not been established in patients coinfected with HBV and HIV-1. Severe acute exacerbations of hepatitis B have been reported in patients who are coinfected with HBV and HIV-1 and have discontinued TRUVADA. Hepatic function should be monitored closely with both clinical and laboratory follow-up for at least several months in patients who are coinfected with HIV-1 and HBV and discontinue TRUVADA. If appropriate, initiation of anti-hepatitis B therapy may be warranted [See Warnings and Precautions (5.2)].

1 INDICATIONS AND USAGE

TRUVADA®, a combination of EMTRIVA® and VIREAD®, is indicated in combination with other antiretroviral agents (such as non-nucleoside reverse transcriptase inhibitors or protease inhibitors) for the treatment of HIV-1 infection in adults and pediatric patients 12 years of age and older.

The following points should be considered when initiating therapy with TRUVADA for the treatment of HIV-1 infection:

- It is not recommended that TRUVADA be used as a component of a triple nucleoside regimen.
- TRUVADA should not be coadministered with ATRIPLA®, EMTRIVA, VIREAD or lamivudine-containing products [See Warnings and Precautions (5.4)].
- In treatment experienced patients, the use of TRUVADA should be guided by laboratory testing and treatment history [See Clinical Pharmacology (12.4)].

2 DOSAGE AND ADMINISTRATION

2.1 Recommended Dose

The dose of TRUVADA for adults and pediatric patients 12 years of age and older with body weight greater than or equal to 35 kg (greater than or equal to 77 lb) is one tablet (containing 200 mg of emtricitabine and 300 mg of tenofovir disoproxil fumarate) once daily taken orally with or without food.

2.2 Dose Adjustment for Renal Impairment

Significantly increased drug exposures occurred when EMTRIVA or VIREAD were administered to subjects with moderate to severe renal impairment [see EMTRIVA or VIREAD Package Insert]. Therefore, the dosing interval of TRUVADA should be adjusted in patients with baseline creatinine clearance 30–49 mL/min using the recommendations in Table 1. These dosing interval recommendations are based on modeling of single-dose pharmacokinetic data in non-HIV infected subjects. The safety and effectiveness of these dosing interval adjustment recommendations have not been clinically evaluated in patients with moderate renal impairment, therefore clinical response to treatment and renal function should be closely monitored in these patients [See Warnings and Precautions (5.3)].

No dose adjustment is necessary for patients with mild renal impairment (creatinine clearance 50–80 mL/min). Routine monitoring of calculated creatinine clearance and serum phosphorus should be performed in patients with mild renal impairment [See Warnings and Precautions (5.3)].

Table 1 Dosage Adjustment for Patients with Altered Creatinine Clearance
 | Creatinine Clearance (mL/min) [Calculated using ideal (lean) body weight]
 | ≥50 | 30–49 | <30 (Including Patients Requiring Hemodialysis)
Recommended Dosing Interval | Every 24 hours | Every 48 hours | TRUVADA should not be administered.

No data are available to make dose recommendations in pediatric patients 12 years of age and older with renal impairment.

3 DOSAGE FORMS AND STRENGTHS

TRUVADA is available as tablets. Each tablet contains 200 mg of emtricitabine and 300 mg of tenofovir disoproxil fumarate (which is equivalent to 245 mg of tenofovir disoproxil). The tablets are blue, capsule-shaped, film-coated, debossed with "GILEAD" on one side and with "701" on the other side.

4 CONTRAINDICATIONS

None.

5 WARNINGS AND PRECAUTIONS

5.1 Lactic Acidosis/Severe Hepatomegaly with Steatosis

Lactic acidosis and severe hepatomegaly with steatosis, including fatal cases, have been reported with the use of nucleoside analogs, including VIREAD, a component of TRUVADA, in combination with other antiretrovirals. A majority of these cases have been in women. Obesity and prolonged nucleoside exposure may be risk factors. Particular caution should be exercised when administering nucleoside analogs to any patient with known risk factors for liver disease; however, cases have also been reported in patients with no known risk factors. Treatment with TRUVADA should be suspended in any patient who develops clinical or laboratory findings suggestive of lactic acidosis or pronounced hepatotoxicity (which may include hepatomegaly and steatosis even in the absence of marked transaminase elevations).

5.2 Patients Coinfected with HIV-1 and HBV

It is recommended that all patients with HIV-1 be tested for the presence of chronic hepatitis B virus (HBV) before initiating antiretroviral therapy. TRUVADA is not approved for the treatment of chronic HBV infection and the safety and efficacy of TRUVADA have not been established in patients coinfected with HBV and HIV-1. Severe acute exacerbations of hepatitis B have been reported in patients who are coinfected with HBV and HIV-1 and have discontinued TRUVADA. In some patients infected with HBV and treated with EMTRIVA, the exacerbations of hepatitis B were associated with liver decompensation and liver failure. Patients who are coinfected with HIV-1 and HBV should be closely monitored with both clinical and laboratory follow up for at least several months after stopping treatment with Truvada. If appropriate, initiation of anti-hepatitis B therapy may be warranted.

5.3 New Onset or Worsening Renal Impairment

Emtricitabine and tenofovir are principally eliminated by the kidney. Renal impairment, including cases of acute renal failure and Fanconi syndrome (renal tubular injury with severe hypophosphatemia), has been reported with the use of VIREAD [See Adverse Reactions (6.2)].

It is recommended that creatinine clearance be calculated in all patients prior to initiating therapy and as clinically appropriate during therapy with TRUVADA. Routine monitoring of calculated creatinine clearance and serum phosphorus should be performed in patients at risk for renal impairment, including patients who have previously experienced renal events while receiving HEPSERA.

Dosing interval adjustment of TRUVADA and close monitoring of renal function are recommended in all patients with creatinine clearance 30–49 mL/min, [See Dosage and Administration (2.2)]. No safety or efficacy data are available in patients with renal impairment who received TRUVADA using these dosing guidelines, so the potential benefit of TRUVADA therapy should be assessed against the potential risk of renal toxicity. TRUVADA should not be administered to patients with creatinine clearance below 30 mL/min or patients requiring hemodialysis.

TRUVADA should be avoided with concurrent or recent use of a nephrotoxic agent.

5.4 Coadministration with Other Products

TRUVADA is a fixed-dose combination of emtricitabine and tenofovir disoproxil fumarate. TRUVADA should not be coadministered with ATRIPLA, EMTRIVA, or VIREAD. Due to similarities between emtricitabine and lamivudine, TRUVADA should not be coadministered with other drugs containing lamivudine, including Combivir (lamivudine/zidovudine), Epivir or Epivir-HBV (lamivudine), Epzicom (abacavir sulfate/lamivudine), or Trizivir (abacavir sulfate/lamivudine/zidovudine).

TRUVADA should not be administered with HEPSERA® (adefovir dipivoxil).

5.5 Decreases in Bone Mineral Density

Assessment of bone mineral density (BMD) should be considered for HIV-1 infected adults and pediatric patients 12 years of age and older who have a history of pathologic bone fracture or other risk factors for osteoporosis or bone loss. Although the effect of supplementation with calcium and vitamin D was not studied, such supplementation may be beneficial for all patients. If bone abnormalities are suspected then appropriate consultation should be obtained.

Tenofovir Disoproxil Fumarate: In a 144-week trial of treatment-naive adult subjects, decreases in BMD were seen at the lumbar spine and hip in both arms of the trial. At Week 144, there was a significantly greater mean percentage decrease from baseline in BMD at the lumbar spine in subjects receiving VIREAD + lamivudine + efavirenz compared with subjects receiving stavudine + lamivudine + efavirenz. Changes in BMD at the hip were similar between the two treatment groups. In both groups, the majority of the reduction in BMD occurred in the first 24–48 weeks of the trial and this reduction was sustained through 144 weeks. Twenty-eight percent of VIREAD-treated subjects vs. 21% of the comparator subjects lost at least 5% of BMD at the spine or 7% of BMD at the hip. Clinically relevant fractures (excluding fingers and toes) were reported in 4 subjects in the VIREAD group and 6 subjects in the comparator group. Tenofovir disoproxil fumarate was associated with significant increases in biochemical markers of bone metabolism (serum bone-specific alkaline phosphatase, serum osteocalcin, serum C-telopeptide, and urinary N-telopeptide), suggesting increased bone turnover. Serum parathyroid hormone levels and 1,25 Vitamin D levels were also higher in subjects receiving VIREAD.

In a clinical trial of HIV-1 infected pediatric subjects 12 years of age and older (Study 321), bone effects were similar to adult subjects. Under normal circumstances BMD increases rapidly in this age group. In this trial, the mean rate of bone gain was less in the VIREAD-treated group compared to the placebo group. Six VIREAD treated subjects and one placebo treated subject had significant (greater than 4%) lumbar spine BMD loss in 48 weeks. Among 28 subjects receiving 96 weeks of VIREAD, Z-scores declined by -0.341 for lumbar spine and -0.458 for total body. Skeletal growth (height) appeared to be unaffected. Markers of bone turnover in VIREAD-treated pediatric subjects 12 years of age and older suggest increased bone turnover, consistent with the effects observed in adults.

The effects of VIREAD-associated changes in BMD and biochemical markers on long-term bone health and future fracture risk are unknown. For additional information, please consult the VIREAD prescribing information.

Cases of osteomalacia (associated with proximal renal tubulopathy and which may contribute to fractures) have been reported in association with the use of VIREAD [See Adverse Reactions (6.2)].

5.6 Fat Redistribution

Redistribution/accumulation of body fat including central obesity, dorsocervical fat enlargement (buffalo hump), peripheral wasting, facial wasting, breast enlargement, and "cushingoid appearance" have been observed in patients receiving antiretroviral therapy. The mechanism and long-term consequences of these events are currently unknown. A causal relationship has not been established.

5.7 Immune Reconstitution Syndrome

Immune reconstitution syndrome has been reported in patients treated with combination antiretroviral therapy, including TRUVADA. During the initial phase of combination antiretroviral treatment, patients whose immune system responds may develop an inflammatory response to indolent or residual opportunistic infections [such as Mycobacterium avium infection, cytomegalovirus, Pneumocystis jirovecii pneumonia (PCP), or tuberculosis], which may necessitate further evaluation and treatment.

5.8 Early Virologic Failure

Clinical trials in HIV-infected subjects have demonstrated that certain regimens that only contain three nucleoside reverse transcriptase inhibitors (NRTI) are generally less effective than triple drug regimens containing two NRTIs in combination with either a non-nucleoside reverse transcriptase inhibitor or a HIV-1 protease inhibitor. In particular, early virological failure and high rates of resistance substitutions have been reported. Triple nucleoside regimens should therefore be used with caution. Patients on a therapy utilizing a triple nucleoside-only regimen should be carefully monitored and considered for treatment modification.

6 ADVERSE REACTIONS

The following adverse reactions are discussed in other sections of the labeling:

- Lactic Acidosis/Severe Hepatomegaly with Steatosis [See Boxed Warning, Warnings and Precautions (5.1)].
- Severe Acute Exacerbations of hepatitis B [See Boxed Warning, Warnings and Precautions (5.2)].
- New Onset or Worsening Renal Impairment [See Warnings and Precautions (5.3)].
- Decreases in Bone Mineral Density [See Warnings and Precautions (5.5)].
- Immune Reconstitution Syndrome [See Warnings and Precautions (5.7)].

6.1 Adverse Reactions from Clinical Trials Experience

Because clinical trials are conducted under widely varying conditions, adverse reaction rates observed in the clinical trials of a drug cannot be directly compared to rates in the clinical trials of another drug and may not reflect the rates observed in practice.

Clinical Trials in Adult Subjects

The most common adverse reactions (incidence greater than or equal to 10%, any severity) occurring in Study 934, an active-controlled clinical trial of efavirenz, emtricitabine, and tenofovir disoproxil fumarate, include diarrhea, nausea, fatigue, headache, dizziness, depression, insomnia, abnormal dreams, and rash. See also Table 2 for the frequency of treatment-emergent adverse reactions (Grade 2–4) occurring in greater than or equal to 5% of subjects treated with efavirenz, emtricitabine, and tenofovir disoproxil fumarate in this trial.

Skin discoloration, manifested by hyperpigmentation on the palms and/or soles was generally mild and asymptomatic. The mechanism and clinical significance are unknown.

Study 934 - Treatment Emergent Adverse Reactions: In Study 934, 511 antiretroviral-naive subjects received either VIREAD + EMTRIVA administered in combination with efavirenz (N=257) or zidovudine/lamivudine administered in combination with efavirenz (N=254). Adverse reactions observed in this trial were generally consistent with those seen in other trials in treatment-experienced or treatment-naive subjects receiving VIREAD and/or EMTRIVA (Table 2).

Table 2 Selected Treatment-Emergent Adverse Reactions [Frequencies of adverse reactions are based on all treatment-emergent adverse events, regardless of relationship to study drug.] (Grades 2–4) Reported in ≥5% in Any Treatment Group in Study 934 (0–144 Weeks)
 | FTC + TDF + EFV [From Weeks 96 to 144 of the trial, subjects received TRUVADA with efavirenz in place of VIREAD + EMTRIVA with efavirenz.] | AZT/3TC + EFV
 | N=257 | N=254
Gastrointestinal Disorder
Diarrhea | 9% | 5%
Nausea | 9% | 7%
Vomiting | 2% | 5%
General Disorders and Administration Site Condition
Fatigue | 9% | 8%
Infections and Infestations
Sinusitis | 8% | 4%
Upper respiratory tract infections | 8% | 5%
Nasopharyngitis | 5% | 3%
Nervous System Disorders
Headache | 6% | 5%
Dizziness | 8% | 7%
Psychiatric Disorders
Depression | 9% | 7%
Insomnia | 5% | 7%
Skin and Subcutaneous Tissue Disorders
Rash event [Rash event includes rash, exfoliative rash, rash generalized, rash macular, rash maculo-papular, rash pruritic, and rash vesicular.] | 7% | 9%

Laboratory Abnormalities: Laboratory abnormalities observed in this trial were generally consistent with those seen in other trials of VIREAD and/or EMTRIVA (Table 3).

Table 3 Significant Laboratory Abnormalities Reported in ≥1% of Subjects in Any Treatment Group in Study 934 (0–144 Weeks)
 | FTC + TDF + EFV [From Weeks 96 to 144 of the trial, subjects received TRUVADA with efavirenz in place of VIREAD + EMTRIVA with efavirenz.] | AZT/3TC + EFV
 | N=257 | N=254
Any ≥ Grade 3 Laboratory Abnormality | 30% | 26%
Fasting Cholesterol (>240 mg/dL) | 22% | 24%
Creatine Kinase (M: >990 U/L) (F: >845 U/L) | 9% | 7%
Serum Amylase (>175 U/L) | 8% | 4%
Alkaline Phosphatase (>550 U/L) | 1% | 0%
AST (M: >180 U/L) (F: >170 U/L) | 3% | 3%
ALT (M: >215 U/L) (F: >170 U/L) | 2% | 3%
Hemoglobin (<8.0 mg/dL) | 0% | 4%
Hyperglycemia (>250 mg/dL) | 2% | 1%
Hematuria (>75 RBC/HPF) | 3% | 2%
Glycosuria (≥3+) | <1% | 1%
Neutrophils (<750/mm^3) | 3% | 5%
Fasting Triglycerides (>750 mg/dL) | 4% | 2%

In addition to the events described above for Study 934, other adverse reactions that occurred in at least 5% of subjects receiving EMTRIVA or VIREAD with other antiretroviral agents in clinical trials include anxiety, arthralgia, increased cough, dyspepsia, fever, myalgia, pain, abdominal pain, back pain, paresthesia, peripheral neuropathy (including peripheral neuritis and neuropathy), pneumonia, and rhinitis.

In addition to the laboratory abnormalities described above for Study 934, Grade 3/4 laboratory abnormalities of increased bilirubin (>2.5 × ULN), increased pancreatic amylase (>2.0 × ULN), increased or decreased serum glucose (<40 or >250 mg/dL), and increased serum lipase (>2.0 × ULN) occurred in up to 3% of subjects treated with EMTRIVA or VIREAD with other antiretroviral agents in clinical trials.

Clinical Trials in Pediatric Subjects 12 Years of Age and Older

Emtricitabine: In addition to the adverse reactions reported in adults, anemia and hyperpigmentation were observed in 7% and 32%, respectively, of pediatric subjects (3 months to less than 18 years of age) who received treatment with EMTRIVA in the larger of two open-label, uncontrolled pediatric trials (N=116). For additional information, please consult the EMTRIVA prescribing information.

Tenofovir Disoproxil Fumarate: In a pediatric clinical trial conducted in subjects 12 to less than 18 years of age, the adverse reactions observed in pediatric subjects who received treatment with VIREAD were consistent with those observed in clinical trials of VIREAD in adults [See Warnings and Precautions (5.5)].

6.2 Postmarketing Experience

The following adverse reactions have been identified during postapproval use of VIREAD. No additional adverse reactions have been identified during postapproval use of EMTRIVA. Because postmarketing reactions are reported voluntarily from a population of uncertain size, it is not always possible to reliably estimate their frequency or establish a causal relationship to drug exposure.

Immune System Disorders
allergic reaction, including angioedema

Metabolism and Nutrition Disorders
lactic acidosis, hypokalemia, hypophosphatemia

Respiratory, Thoracic, and Mediastinal Disorders
dyspnea

Gastrointestinal Disorders
pancreatitis, increased amylase, abdominal pain

Hepatobiliary Disorders
hepatic steatosis, hepatitis, increased liver enzymes (most commonly AST, ALT gamma GT)

Skin and Subcutaneous Tissue Disorders
rash

Musculoskeletal and Connective Tissue Disorders
rhabdomyolysis, osteomalacia (manifested as bone pain and which may contribute to fractures), muscular weakness, myopathy

Renal and Urinary Disorders
acute renal failure, renal failure, acute tubular necrosis, Fanconi syndrome, proximal renal tubulopathy, interstitial nephritis (including acute cases), nephrogenic diabetes insipidus, renal insufficiency, increased creatinine, proteinuria, polyuria

General Disorders and Administration Site Conditions
asthenia

The following adverse reactions, listed under the body system headings above, may occur as a consequence of proximal renal tubulopathy: rhabdomyolysis, osteomalacia, hypokalemia, muscular weakness, myopathy, hypophosphatemia.

7 DRUG INTERACTIONS

No drug interaction trials have been conducted using TRUVADA tablets. Drug interaction trials have been conducted with emtricitabine and tenofovir disoproxil fumarate, the components of TRUVADA. This section describes clinically relevant drug interactions observed with emtricitabine and tenofovir disoproxil fumarate [See Clinical Pharmacology (12.3)].

7.1 Didanosine

Coadministration of TRUVADA and didanosine should be undertaken with caution and patients receiving this combination should be monitored closely for didanosine-associated adverse reactions. Didanosine should be discontinued in patients who develop didanosine-associated adverse reactions.

When tenofovir disoproxil fumarate was administered with didanosine the Cmax and AUC of didanosine administered as either the buffered or enteric-coated formulation increased significantly [See Clinical Pharmacology (12.3)]. The mechanism of this interaction is unknown. Higher didanosine concentrations could potentiate didanosine-associated adverse reactions, including pancreatitis, and neuropathy. Suppression of CD4^+ cell counts has been observed in patients receiving tenofovir DF with didanosine 400 mg daily.

In patients weighing greater than 60 kg, the didanosine dose should be reduced to 250 mg when it is coadministered with TRUVADA. Data are not available to recommend a dose adjustment of didanosine for adult or pediatric patients weighing less than 60 kg. When coadministered, TRUVADA and Videx EC may be taken under fasted conditions or with a light meal (less than 400 kcal, 20% fat). Coadministration of didanosine buffered tablet formulation with TRUVADA should be under fasted conditions.

7.2 Atazanavir

Atazanavir has been shown to increase tenofovir concentrations [See Clinical Pharmacology (12.3)]. The mechanism of this interaction is unknown. Patients receiving atazanavir and TRUVADA should be monitored for TRUVADA-associated adverse reactions. TRUVADA should be discontinued in patients who develop TRUVADA-associated adverse reactions.

Tenofovir decreases the AUC and Cmin of atazanavir [See Clinical Pharmacology (12.3)]. When coadministered with TRUVADA, it is recommended that atazanavir 300 mg is given with ritonavir 100 mg. Atazanavir without ritonavir should not be coadministered with TRUVADA.

7.3 Lopinavir/Ritonavir

Lopinavir/ritonavir has been shown to increase tenofovir concentrations [See Clinical Pharmacology (12.3)]. The mechanism of this interaction is unknown. Patients receiving lopinavir/ritonavir and TRUVADA should be monitored for TRUVADA-associated adverse reactions. TRUVADA should be discontinued in patients who develop TRUVADA-associated adverse reactions.

7.4 Drugs Affecting Renal Function

Emtricitabine and tenofovir are primarily excreted by the kidneys by a combination of glomerular filtration and active tubular secretion [See Clinical Pharmacology (12.3)]. No drug-drug interactions due to competition for renal excretion have been observed; however, coadministration of TRUVADA with drugs that are eliminated by active tubular secretion may increase concentrations of emtricitabine, tenofovir, and/or the coadministered drug. Some examples include, but are not limited to acyclovir, adefovir dipivoxil, cidofovir, ganciclovir, valacyclovir, and valganciclovir. Drugs that decrease renal function may increase concentrations of emtricitabine and/or tenofovir.

8 USE IN SPECIFIC POPULATIONS

8.1 Pregnancy

TERATOGENIC EFFECTS

Pregnancy Category B

Emtricitabine: The incidence of fetal variations and malformations was not increased in embryofetal toxicity studies performed with emtricitabine in mice at exposures (AUC) approximately 60-fold higher and in rabbits at approximately 120-fold higher than human exposures at the recommended daily dose.

Tenofovir Disoproxil Fumarate: Reproduction studies have been performed in rats and rabbits at doses up to 14 and 19 times the human dose based on body surface area comparisons and revealed no evidence of impaired fertility or harm to the fetus due to tenofovir.

There are, however, no adequate and well-controlled trials in pregnant women. Because animal reproduction studies are not always predictive of human response, TRUVADA should be used during pregnancy only if clearly needed.

Antiretroviral Pregnancy Registry: To monitor fetal outcomes of pregnant women exposed to TRUVADA, an Antiretroviral Pregnancy Registry has been established. Healthcare providers are encouraged to register patients by calling 1-800-258-4263.

8.3 Nursing Mothers

Nursing Mothers: The Centers for Disease Control and Prevention recommend that HIV-1 infected mothers not breast-feed their infants to avoid risking postnatal transmission of HIV-1. Studies in rats have demonstrated that tenofovir is secreted in milk. It is not known whether tenofovir is excreted in human milk. It is not known whether emtricitabine is excreted in human milk. Because of both the potential for HIV-1 transmission and the potential for serious adverse reactions in nursing infants, mothers should be instructed not to breast-feed if they are receiving TRUVADA.

8.4 Pediatric Use

Truvada should only be administered to pediatric patients 12 years of age and older with body weight greater than or equal to 35 kg (greater than or equal to 77 lb) because it is a fixed-dose combination tablet containing a component, VIREAD, for which safety and efficacy have not been established in pediatric patients less than 12 years of age or weighing less than 35 kg (less than 77 lb) [See Warnings and Precautions (5.5), Adverse Reactions (6.1) and Clinical Pharmacology (12.3)].

8.5 Geriatric Use

Clinical trials of EMTRIVA or VIREAD did not include sufficient numbers of subjects aged 65 and over to determine whether they respond differently from younger subjects. In general, dose selection for the elderly patients should be cautious, keeping in mind the greater frequency of decreased hepatic, renal, or cardiac function, and of concomitant disease or other drug therapy.

8.6 Patients with Impaired Renal Function

It is recommended that the dosing interval for TRUVADA be modified in patients with creatinine clearance 30–49 mL/min. TRUVADA should not be used in patients with creatinine clearance below 30 mL/min and in patients with end-stage renal disease requiring dialysis [See Dosage and Administration (2.2)].

10 OVERDOSAGE

If overdose occurs the patient must be monitored for evidence of toxicity, and standard supportive treatment applied as necessary.

Emtricitabine: Limited clinical experience is available at doses higher than the therapeutic dose of EMTRIVA. In one clinical pharmacology trials single doses of emtricitabine 1200 mg were administered to 11 subjects. No severe adverse reactions were reported.

Hemodialysis treatment removes approximately 30% of the emtricitabine dose over a 3-hour dialysis period starting within 1.5 hours of emtricitabine dosing (blood flow rate of 400 mL/min and a dialysate flow rate of 600 mL/min). It is not known whether emtricitabine can be removed by peritoneal dialysis.

Tenofovir Disoproxil Fumarate: Limited clinical experience at doses higher than the therapeutic dose of VIREAD 300 mg is available. In one trial, 600 mg tenofovir disoproxil fumarate was administered to 8 subjects orally for 28 days, and no severe adverse reactions were reported. The effects of higher doses are not known.

Tenofovir is efficiently removed by hemodialysis with an extraction coefficient of approximately 54%. Following a single 300 mg dose of VIREAD, a four-hour hemodialysis session removed approximately 10% of the administered tenofovir dose.

11 DESCRIPTION

TRUVADA tablets are fixed dose combination tablets containing emtricitabine and tenofovir disoproxil fumarate. EMTRIVA is the brand name for emtricitabine, a synthetic nucleoside analog of cytidine. Tenofovir disoproxil fumarate (tenofovir DF) is converted in vivo to tenofovir, an acyclic nucleoside phosphonate (nucleotide) analog of adenosine 5'-monophosphate. Both emtricitabine and tenofovir exhibit inhibitory activity against HIV-1 reverse transcriptase.

Emtricitabine: The chemical name of emtricitabine is 5-fluoro-1-(2R,5S)-[2-(hydroxymethyl)-1,3-oxathiolan-5-yl]cytosine. Emtricitabine is the (-) enantiomer of a thio analog of cytidine, which differs from other cytidine analogs in that it has a fluorine in the 5-position.

It has a molecular formula of C8H10FN3O3S and a molecular weight of 247.24. It has the following structural formula:

Emtricitabine is a white to off-white crystalline powder with a solubility of approximately 112 mg/mL in water at 25 °C. The partition coefficient (log p) for emtricitabine is -0.43 and the pKa is 2.65.

Tenofovir Disoproxil Fumarate: Tenofovir disoproxil fumarate is a fumaric acid salt of the bis-isopropoxycarbonyloxymethyl ester derivative of tenofovir. The chemical name of tenofovir disoproxil fumarate is 9-[(R)-2 [[bis[[(isopropoxycarbonyl)oxy]- methoxy]phosphinyl]methoxy]propyl]adenine fumarate (1:1). It has a molecular formula of C19H30N5O10P • C4H4O4 and a molecular weight of 635.52. It has the following structural formula:

Tenofovir disoproxil fumarate is a white to off-white crystalline powder with a solubility of 13.4 mg/mL in water at 25 °C. The partition coefficient (log p) for tenofovir disoproxil is 1.25 and the pKa is 3.75. All dosages are expressed in terms of tenofovir disoproxil fumarate except where otherwise noted.

TRUVADA tablets are for oral administration. Each film-coated tablet contains 200 mg of emtricitabine and 300 mg of tenofovir disoproxil fumarate, (which is equivalent to 245 mg of tenofovir disoproxil), as active ingredients. The tablets also include the following inactive ingredients: croscarmellose sodium, lactose monohydrate, magnesium stearate, microcrystalline cellulose, and pregelatinized starch (gluten free). The tablets are coated with Opadry II Blue Y-30-10701, which contains FD&C Blue #2 aluminum lake, hydroxypropyl methylcellulose 2910, lactose monohydrate, titanium dioxide, and triacetin.

12 CLINICAL PHARMACOLOGY

For additional information on Mechanism of Action, Antiviral Activity, Resistance and Cross Resistance, please consult the EMTRIVA and VIREAD prescribing information.

12.1 Mechanism of Action

TRUVADA is a fixed-dose combination of antiviral drugs emtricitabine and tenofovir disoproxil fumarate. [See Clinical Pharmacology (12.4)].

12.3 Pharmacokinetics

TRUVADA: One TRUVADA tablet was bioequivalent to one EMTRIVA capsule (200 mg) plus one VIREAD tablet (300 mg) following single-dose administration to fasting healthy subjects (N=39).

Emtricitabine: The pharmacokinetic properties of emtricitabine are summarized in Table 4. Following oral administration of EMTRIVA, emtricitabine is rapidly absorbed with peak plasma concentrations occurring at 1–2 hours post-dose. Less than 4% of emtricitabine binds to human plasma proteins in vitro and the binding is independent of concentration over the range of 0.02–200 µg/mL. Following administration of radiolabelled emtricitabine, approximately 86% is recovered in the urine and 13% is recovered as metabolites. The metabolites of emtricitabine include 3'-sulfoxide diastereomers and their glucuronic acid conjugate. Emtricitabine is eliminated by a combination of glomerular filtration and active tubular secretion. Following a single oral dose of EMTRIVA, the plasma emtricitabine half-life is approximately 10 hours.

Tenofovir Disoproxil Fumarate: The pharmacokinetic properties of tenofovir disoproxil fumarate are summarized in Table 4. Following oral administration of VIREAD, maximum tenofovir serum concentrations are achieved in 1.0 ± 0.4 hour. Less than 0.7% of tenofovir binds to human plasma proteins in vitro and the binding is independent of concentration over the range of 0.01–25 µg/mL. Approximately 70–80% of the intravenous dose of tenofovir is recovered as unchanged drug in the urine. Tenofovir is eliminated by a combination of glomerular filtration and active tubular secretion. Following a single oral dose of VIREAD, the terminal elimination half-life of tenofovir is approximately 17 hours.

Table 4 Single Dose Pharmacokinetic Parameters for Emtricitabine and Tenofovir in Adults [NC = Not calculated]
 | Emtricitabine | Tenofovir
Fasted Oral Bioavailability [Median (range)] (%) | 92 (83.1–106.4) | 25 (NC–45.0)
Plasma Terminal Elimination Half-Life (hr) | 10 (7.4–18.0) | 17 (12.0–25.7)
Cmax [Mean (± SD)] (µg/mL) | 1.8 ± 0.72 [Data presented as steady state values.] | 0.30 ± 0.09
AUC (µg∙hr/mL) | 10.0 ± 3.12 | 2.29 ± 0.69
CL/F (mL/min) | 302 ± 94 | 1043 ± 115
CLrenal (mL/min) | 213 ± 89 | 243 ± 33

Effects of Food on Oral Absorption

TRUVADA may be administered with or without food. Administration of TRUVADA following a high fat meal (784 kcal; 49 grams of fat) or a light meal (373 kcal; 8 grams of fat) delayed the time of tenofovir Cmax by approximately 0.75 hour. The mean increases in tenofovir AUC and Cmax were approximately 35% and 15%, respectively, when administered with a high fat or light meal, compared to administration in the fasted state. In previous safety and efficacy trials, VIREAD (tenofovir) was taken under fed conditions. Emtricitabine systemic exposures (AUC and Cmax) were unaffected when TRUVADA was administered with either a high fat or a light meal.

Special Populations

Race

Emtricitabine: No pharmacokinetic differences due to race have been identified following the administration of EMTRIVA.

Tenofovir Disoproxil Fumarate: There were insufficient numbers from racial and ethnic groups other than Caucasian to adequately determine potential pharmacokinetic differences among these populations following the administration of VIREAD.

Gender

Emtricitabine and Tenofovir Disoproxil Fumarate: Emtricitabine and tenofovir pharmacokinetics are similar in male and female subjects.

Pediatric Patients

TRUVADA should not be administered to pediatric patients less than 12 years of age or weighing less than 35 kg (less than 77 lb).

Emtricitabine: The pharmacokinetics of emtricitabine at steady state were determined in 27 HIV-1-infected pediatric subjects 13 to 17 years of age receiving a daily dose of 6 mg/kg up to a maximum dose of 240 mg oral solution or a 200 mg capsule; 26 of 27 subjects in this age group received the 200 mg EMTRIVA capsule. Mean (± SD) Cmax and AUC were 2.7 ± 0.9 μg/mL and 12.6 ± 5.4 μg•hr/mL, respectively. Exposures achieved in pediatric subjects 12 to less than 18 years of age were similar to those achieved in adults receiving a once daily dose of 200 mg.

Tenofovir Disoproxil Fumarate: Steady-state pharmacokinetics of tenofovir were evaluated in 8 HIV-1 infected pediatric subjects (12 to less than 18 years). Mean (± SD) Cmax and AUCtau are 0.38 ± 0.13 μg/mL and 3.39 ± 1.22 μg•hr/mL, respectively. Tenofovir exposure achieved in these pediatric subjects receiving oral daily doses of VIREAD 300 mg was similar to exposures achieved in adults receiving once-daily doses of VIREAD 300 mg.

Geriatric Patients

Pharmacokinetics of emtricitabine and tenofovir have not been fully evaluated in the elderly (65 years of age and older).

Patients with Impaired Renal Function

The pharmacokinetics of emtricitabine and tenofovir are altered in subjects with renal impairment [See Warnings and Precautions (5.3)]. In adult subjects with creatinine clearance below 50 mL/min, Cmax, and AUC0–∞ of emtricitabine and tenofovir were increased. It is recommended that the dosing interval for TRUVADA be modified in patients with creatinine clearance 30–49 mL/min. TRUVADA should not be used in patients with creatinine clearance below 30 mL/min and in patients with end-stage renal disease requiring dialysis [See Dosage and Administration (2.2)].

Patients with Hepatic Impairment

The pharmacokinetics of tenofovir following a 300 mg dose of VIREAD have been studied in non-HIV infected subjects with moderate to severe hepatic impairment. There were no substantial alterations in tenofovir pharmacokinetics in subjects with hepatic impairment compared with unimpaired subjects. The pharmacokinetics of TRUVADA or emtricitabine have not been studied in subjects with hepatic impairment; however, emtricitabine is not significantly metabolized by liver enzymes, so the impact of liver impairment should be limited.

Assessment of Drug Interactions

The steady state pharmacokinetics of emtricitabine and tenofovir were unaffected when emtricitabine and tenofovir disoproxil fumarate were administered together versus each agent dosed alone.

In vitro studies and clinical pharmacokinetic drug-drug interaction trials have shown that the potential for CYP mediated interactions involving emtricitabine and tenofovir with other medicinal products is low.

No clinically significant drug interactions have been observed between emtricitabine and famciclovir, indinavir, stavudine, tenofovir disoproxil fumarate, and zidovudine (see Tables 5 and 6). Similarly, no clinically significant drug interactions have been observed between tenofovir disoproxil fumarate and abacavir, efavirenz, emtricitabine, entecavir, indinavir, lamivudine, lopinavir/ritonavir, methadone, nelfinavir, oral contraceptives, ribavirin, saquinavir/ritonavir, and tacrolimus in trials conducted in healthy volunteers (see Tables 7 and 8).

Table 5 Drug Interactions: Changes in Pharmacokinetic Parameters for Emtricitabine in the Presence of the Coadministered Drug [All interaction trials conducted in healthy volunteers.]
Coadministered Drug | Dose of Coadministered Drug (mg) | Emtricitabine Dose (mg) | N | % Change of Emtricitabine Pharmacokinetic Parameters [↑ = Increase; ↓ = Decrease; = No Effect; NA = Not Applicable] (90% CI)
Coadministered Drug | Dose of Coadministered Drug (mg) | Emtricitabine Dose (mg) | N | Cmax | AUC | Cmin
Tenofovir DF | 300 once daily × 7 days | 200 once daily × 7 days | 17 |  |  | ↑ 20 (↑ 12 to ↑ 29)
Zidovudine | 300 twice daily × 7 days | 200 once daily × 7 days | 27
Indinavir | 800 × 1 | 200 × 1 | 12 |  |  | NA
Famciclovir | 500 × 1 | 200 × 1 | 12 |  |  | NA
Stavudine | 40 × 1 | 200 × 1 | 6 |  |  | NA

Table 6 Drug Interactions: Changes in Pharmacokinetic Parameters for Coadministered Drug in the Presence of Emtricitabine [All interaction trials conducted in healthy volunteers.]
Coadministered Drug | Dose of Coadministered Drug (mg) | Emtricitabine Dose (mg) | N | % Change of Coadministered Drug Pharmacokinetic Parameters [↑ = Increase; ↓ = Decrease; = No Effect; NA = Not Applicable] (90% CI)
Coadministered Drug | Dose of Coadministered Drug (mg) | Emtricitabine Dose (mg) | N | Cmax | AUC | Cmin
Tenofovir DF | 300 once daily × 7 days | 200 once daily × 7 days | 17
Zidovudine | 300 twice daily × 7 days | 200 once daily × 7 days | 27 | ↑ 17 (↑ 0 to ↑ 38) | ↑ 13 (↑ 5 to ↑ 20)
Indinavir | 800 × 1 | 200 × 1 | 12 |  |  | NA
Famciclovir | 500 × 1 | 200 × 1 | 12 |  |  | NA
Stavudine | 40 × 1 | 200 × 1 | 6 |  |  | NA

Table 7 Drug Interactions: Changes in Pharmacokinetic Parameters for Tenofovir [Subjects received VIREAD 300 mg once daily.] in the Presence of the Coadministered Drug
Coadministered Drug | Dose of Coadministered Drug (mg) | N | % Change of Tenofovir Pharmacokinetic Parameters [Increase = ↑; Decrease = ↓; No Effect = ; NC = Not Calculated] (90% CI)
Coadministered Drug | Dose of Coadministered Drug (mg) | N | Cmax | AUC | Cmin
Abacavir | 300 once | 8 |  |  | NC
Atazanavir [Reyataz Prescribing Information] | 400 once daily × 14 days | 33 | ↑ 14 (↑ 8 to ↑ 20) | ↑ 24 (↑ 21 to ↑ 28) | ↑ 22 (↑ 15 to ↑ 30)
Didanosine (enteric-coated) | 400 once | 25
Didanosine (buffered) | 250 or 400 once daily × 7 days | 14
Efavirenz | 600 once daily × 14 days | 29
Emtricitabine | 200 once daily × 7 days | 17
Entecavir | 1 mg once daily × 10 days | 28
Indinavir | 800 three times daily × 7 days | 13 | ↑ 14 (↓ 3 to ↑ 33)
Lamivudine | 150 twice daily × 7 days | 15
Lopinavir/Ritonavir | 400/100 twice daily × 14 days | 24 |  | ↑ 32 (↑ 25 to ↑ 38) | ↑ 51 (↑ 37 to ↑ 66)
Nelfinavir | 1250 twice daily × 14 days | 29
Saquinavir/Ritonavir | 1000/100 twice daily × 14 days | 35 |  |  | ↑ 23 (↑ 16 to ↑ 30)
Tacrolimus | 0.05 mg/kg twice daily × 7 days | 21 | ↑ 13 (↑ 1 to ↑ 27)

Table 8 Drug Interactions: Changes in Pharmacokinetic Parameters for Coadministered Drug in the Presence of Tenofovir
Coadministered Drug | Dose of Coadministered Drug (mg) | N | % Change of Coadministered Drug Pharmacokinetic Parameters [Increase = ↑; Decrease = ↓; No Effect = ; NA = Not Applicable] (90% CI)
Coadministered Drug | Dose of Coadministered Drug (mg) | N | Cmax | AUC | Cmin
Abacavir | 300 once | 8 | ↑ 12 (↓ 1 to ↑ 26) |  | NA
Atazanavir [Reyataz Prescribing Information] | 400 once daily × 14 days | 34 | ↓ 21 (↓ 27 to ↓ 14) | ↓ 25 (↓ 30 to ↓ 19) | ↓ 40 (↓ 48 to ↓ 32)
Atazanavir | Atazanavir/Ritonavir 300/100 once daily × 42 days | 10 | ↓ 28 (↓ 50 to ↑ 5) | ↓ 25 [In HIV-infected subjects, addition of tenofovir DF to atazanavir 300 mg plus ritonavir 100 mg, resulted in AUC and Cmin values of atazanavir that were 2.3 and 4-fold higher than the respective values observed for atazanavir 400 mg when given alone.] (↓ 42 to ↓ 3) | ↓ 23 (↓ 46 to ↑ 10)
Efavirenz | 600 once daily × 14 days | 30
Emtricitabine | 200 once daily × 7 days | 17 |  |  | ↑ 20 (↑ 12 to ↑ 29)
Indinavir | 800 three times daily × 7 days | 12 | ↓ 11 (↓ 30 to ↑ 12)
Entecavir | 1 mg once daily × 10 days | 28 |  | ↑ 13 (↑ 11 to ↑ 15)
Lamivudine | 150 twice daily × 7 days | 15 | ↓ 24 (↓ 34 to ↓ 12)
Lopinavir | Lopinavir/Ritonavir 400/100 twice daily × 14 days | 24
Ritonavir | Lopinavir/Ritonavir 400/100 twice daily × 14 days | 24
Methadone [R-(active), S- and total methadone exposures were equivalent when dosed alone or with VIREAD.] | 40–110 once daily × 14 days [Individual subjects were maintained on their stable methadone dose. No pharmacodynamic alterations (opiate toxicity or withdrawal signs or symptoms) were reported.] | 13
Nelfinavir | 1250 twice daily × 14 days | 29
M8 metabolite | 1250 twice daily × 14 days | 29
Oral Contraceptives [Ethinyl estradiol and 17-deacetyl norgestimate (pharmacologically active metabolite) exposures were equivalent when dosed alone or with VIREAD.] | Ethinyl Estradiol/ Norgestimate (Ortho-Tricyclen) Once daily × 7 days | 20
Ribavirin | 600 once | 22 |  |  | NA
Saquinavir | Saquinavir/Ritonavir 1000/100 twice daily × 14 days | 32 | ↑ 22 (↑ 6 to ↑41) | ↑ 29 [Increases in AUC and Cmin are not expected to be clinically relevant; hence no dose adjustments are required when tenofovir DF and ritonavir-boosted saquinavir are coadministered.] (↑ 12 to ↑ 48) | ↑ 47 (↑ 23 to ↑ 76)
Ritonavir | Saquinavir/Ritonavir 1000/100 twice daily × 14 days | 32 |  |  | ↑ 23 (↑ 3 to ↑ 46)
Tacrolimus | 0.05 mg/kg twice daily × 7 days | 21

Following multiple dosing to HIV-negative subjects receiving either chronic methadone maintenance therapy or oral contraceptives, or single doses of ribavirin, steady state tenofovir pharmacokinetics were similar to those observed in previous trials, indicating lack of clinically significant drug interactions between these agents and VIREAD.

Coadministration of tenofovir disoproxil fumarate with didanosine results in changes in the pharmacokinetics of didanosine that may be of clinical significance. Table 9 summarizes the effects of tenofovir disoproxil fumarate on the pharmacokinetics of didanosine. Concomitant dosing of tenofovir disoproxil fumarate with didanosine buffered tablets or enteric-coated capsules significantly increases the Cmax and AUC of didanosine. When didanosine 250 mg enteric-coated capsules were administered with tenofovir disoproxil fumarate, systemic exposures of didanosine were similar to those seen with the 400 mg enteric-coated capsules alone under fasted conditions. The mechanism of this interaction is unknown. See Drug Interactions (7.1) regarding use of didanosine with VIREAD.

Table 9 Drug Interactions: Pharmacokinetic Parameters for Didanosine in the Presence of VIREAD
Didanosine [Administration with food was with a light meal (~373 kcal, 20% fat).] Dose (mg)/Method of Administration | VIREAD Method of Administration | N | % Difference (90% CI) vs. Didanosine 400 mg Alone, Fasted [Increase = ↑; Decrease = ↓; No Effect =]
Didanosine [Administration with food was with a light meal (~373 kcal, 20% fat).] Dose (mg)/Method of Administration | VIREAD Method of Administration | N | Cmax | AUC
Buffered tablets
400 once daily [Includes 4 subjects weighing <60 kg receiving ddI 250 mg.] × 7 days | Fasted 1 hour after didanosine | 14 | ↑ 28 (↑ 11 to ↑ 48) | ↑ 44 (↑ 31 to ↑ 59)
Enteric coated capsules
400 once, fasted | With food, 2 hours after didanosine | 26 | ↑ 48 (↑ 25 to ↑ 76) | ↑ 48 (↑ 31 to ↑ 67)
400 once, with food | Simultaneously with didanosine | 26 | ↑ 64 (↑ 41 to ↑ 89) | ↑ 60 (↑ 44 to ↑ 79)
250 once, fasted | With food, 2 hours after didanosine | 28 | ↓ 10 (↓ 22 to ↑ 3)
250 once, fasted | Simultaneously with didanosine | 28 |  | ↑ 14 (0 to ↑ 31)
250 once, with food | Simultaneously with didanosine | 28 | ↓ 29 (↓ 39 to ↓ 18) | ↓ 11 (↓ 23 to ↑ 2)

12.4 Microbiology

Mechanism of Action

Emtricitabine: Emtricitabine, a synthetic nucleoside analog of cytidine, is phosphorylated by cellular enzymes to form emtricitabine 5'-triphosphate. Emtricitabine 5'-triphosphate inhibits the activity of the HIV-1 reverse transcriptase (RT) by competing with the natural substrate deoxycytidine 5'-triphosphate and by being incorporated into nascent viral DNA which results in chain termination. Emtricitabine 5'-triphosphate is a weak inhibitor of mammalian DNA polymerase α, β, ε and mitochondrial DNA polymerase γ.

Tenofovir Disoproxil Fumarate: Tenofovir disoproxil fumarate is an acyclic nucleoside phosphonate diester analog of adenosine monophosphate. Tenofovir disoproxil fumarate requires initial diester hydrolysis for conversion to tenofovir and subsequent phosphorylations by cellular enzymes to form tenofovir diphosphate. Tenofovir diphosphate inhibits the activity of HIV-1 RT by competing with the natural substrate deoxyadenosine 5'-triphosphate and, after incorporation into DNA, by DNA chain termination. Tenofovir diphosphate is a weak inhibitor of mammalian DNA polymerases α, β, and mitochondrial DNA polymerase γ.

Antiviral Activity

Emtricitabine and Tenofovir Disoproxil Fumarate: In combination studies evaluating the cell culture antiviral activity of emtricitabine and tenofovir together, synergistic antiviral effects were observed.

Emtricitabine: The antiviral activity of emtricitabine against laboratory and clinical isolates of HIV-1 was assessed in lymphoblastoid cell lines, the MAGI-CCR5 cell line, and peripheral blood mononuclear cells. The 50% effective concentration (EC50) values for emtricitabine were in the range of 0.0013–0.64 µM (0.0003–0.158 µg/mL). In drug combination studies of emtricitabine with nucleoside reverse transcriptase inhibitors (abacavir, lamivudine, stavudine, zalcitabine, zidovudine), non-nucleoside reverse transcriptase inhibitors (delavirdine, efavirenz, nevirapine), and protease inhibitors (amprenavir, nelfinavir, ritonavir, saquinavir), additive to synergistic effects were observed. Emtricitabine displayed antiviral activity in cell culture against HIV-1 clades A, B, C, D, E, F, and G (EC50 values ranged from 0.007–0.075 µM) and showed strain specific activity against HIV-2 (EC50 values ranged from 0.007–1.5 µM).

Tenofovir Disoproxil Fumarate: The antiviral activity of tenofovir against laboratory and clinical isolates of HIV-1 was assessed in lymphoblastoid cell lines, primary monocyte/macrophage cells and peripheral blood lymphocytes. The EC50 values for tenofovir were in the range of 0.04–8.5 µM. In drug combination studies of tenofovir with nucleoside reverse transcriptase inhibitors (abacavir, didanosine, lamivudine, stavudine, zalcitabine, zidovudine), non-nucleoside reverse transcriptase inhibitors (delavirdine, efavirenz, nevirapine), and protease inhibitors (amprenavir, indinavir, nelfinavir, ritonavir, saquinavir), additive to synergistic effects were observed. Tenofovir displayed antiviral activity in cell culture against HIV-1 clades A, B, C, D, E, F, G and O (EC50 values ranged from 0.5–2.2 µM) and showed strain specific activity against HIV-2 (EC50 values ranged from 1.6 µM to 5.5 µM).

Resistance

Emtricitabine and Tenofovir Disoproxil Fumarate: HIV-1 isolates with reduced susceptibility to the combination of emtricitabine and tenofovir have been selected in cell culture. Genotypic analysis of these isolates identified the M184V/I and/or K65R amino acid substitutions in the viral RT.

In a clinical trial of treatment-naive subjects [Study 934, see Clinical Studies (14.1)], resistance analysis was performed on HIV-1 isolates from all confirmed virologic failure subjects with greater than 400 copies/mL of HIV-1 RNA at Week 144 or early discontinuation. Development of efavirenz resistance-associated substitutions occurred most frequently and was similar between the treatment arms. The M184V amino acid substitution, associated with resistance to EMTRIVA and lamivudine, was observed in 2/19 analyzed subjects isolates in the EMTRIVA + VIREAD group and in 10/29 analyzed subjects isolates in the zidovudine/lamivudine group. Through 144 weeks of Study 934, no subjects have developed a detectable K65R substitution in their HIV-1 as analyzed through standard genotypic analysis.

Emtricitabine: Emtricitabine-resistant isolates of HIV-1 have been selected in cell culture and in vivo. Genotypic analysis of these isolates showed that the reduced susceptibility to emtricitabine was associated with a substitution in the HIV-1 RT gene at codon 184 which resulted in an amino acid substitution of methionine by valine or isoleucine (M184V/I).

Tenofovir Disoproxil Fumarate: HIV-1 isolates with reduced susceptibility to tenofovir have been selected in cell culture. These viruses expressed a K65R substitution in RT and showed a 2–4 fold reduction in susceptibility to tenofovir.

In treatment-naive subjects, isolates from 8/47 (17%) analyzed subjects developed the K65R substitution in the VIREAD arm through 144 weeks; 7 occurred in the first 48 weeks of treatment and 1 at Week 96. In treatment-experienced subjects, 14/304 (5%) isolates from subjects failing VIREAD through Week 96 showed greater than 1.4 fold (median 2.7) reduced susceptibility to tenofovir. Genotypic analysis of the resistant isolates showed a substitution in the HIV-1 RT gene resulting in the K65R amino acid substitution.

Cross Resistance

Emtricitabine and Tenofovir Disoproxil Fumarate: Cross-resistance among certain nucleoside reverse transcriptase inhibitors (NRTIs) has been recognized. The M184V/I and/or K65R substitutions selected in cell culture by the combination of emtricitabine and tenofovir are also observed in some HIV-1 isolates from subjects failing treatment with tenofovir in combination with either lamivudine or emtricitabine, and either abacavir or didanosine. Therefore, cross-resistance among these drugs may occur in patients whose virus harbors either or both of these amino acid substitutions.

Emtricitabine: Emtricitabine-resistant isolates (M184V/I) were cross-resistant to lamivudine and zalcitabine but retained susceptibility in cell culture to didanosine, stavudine, tenofovir, zidovudine, and NNRTIs (delavirdine, efavirenz, and nevirapine). HIV-1 isolates containing the K65R substitution, selected in vivo by abacavir, didanosine, tenofovir, and zalcitabine, demonstrated reduced susceptibility to inhibition by emtricitabine. Viruses harboring substitutions conferring reduced susceptibility to stavudine and zidovudine (M41L, D67N, K70R, L210W, T215Y/F, K219Q/E), or didanosine (L74V) remained sensitive to emtricitabine. HIV-1 containing the K103N substitution associated with resistance to NNRTIs was susceptible to emtricitabine.

Tenofovir Disoproxil Fumarate: HIV-1 isolates from subjects (N=20) whose HIV-1 expressed a mean of 3 zidovudine-associated RT amino acid substitutions (M41L, D67N, K70R, L210W, T215Y/F, or K219Q/E/N) showed a 3.1-fold decrease in the susceptibility to tenofovir. Subjects whose virus expressed an L74V substitution without zidovudine resistance associated substitutions (N=8) had reduced response to VIREAD. Limited data are available for patients whose virus expressed a Y115F substitution (N=3), Q151M substitution (N=2), or T69 insertion (N=4), all of whom had a reduced response.

13 NONCLINICAL TOXICOLOGY

13.1 Carcinogenesis, Mutagenesis, Impairment of Fertility

Emtricitabine: In long-term oral carcinogenicity studies of emtricitabine, no drug-related increases in tumor incidence were found in mice at doses up to 750 mg/kg/day (26 times the human systemic exposure at the therapeutic dose of 200 mg/day) or in rats at doses up to 600 mg/kg/day (31 times the human systemic exposure at the therapeutic dose).

Emtricitabine was not genotoxic in the reverse mutation bacterial test (Ames test), mouse lymphoma or mouse micronucleus assays.

Emtricitabine did not affect fertility in male rats at approximately 140-fold or in male and female mice at approximately 60-fold higher exposures (AUC) than in humans given the recommended 200 mg daily dose. Fertility was normal in the offspring of mice exposed daily from before birth (in utero) through sexual maturity at daily exposures (AUC) of approximately 60-fold higher than human exposures at the recommended 200 mg daily dose.

Tenofovir Disoproxil Fumarate: Long-term oral carcinogenicity studies of tenofovir disoproxil fumarate in mice and rats were carried out at exposures up to approximately 16 times (mice) and 5 times (rats) those observed in humans at the therapeutic dose for HIV-1 infection. At the high dose in female mice, liver adenomas were increased at exposures 16 times that in humans. In rats, the study was negative for carcinogenic findings at exposures up to 5 times that observed in humans at the therapeutic dose.

Tenofovir disoproxil fumarate was mutagenic in the in vitro mouse lymphoma assay and negative in an in vitro bacterial mutagenicity test (Ames test). In an in vivo mouse micronucleus assay, tenofovir disoproxil fumarate was negative when administered to male mice.

There were no effects on fertility, mating performance or early embryonic development when tenofovir disoproxil fumarate was administered to male rats at a dose equivalent to 10 times the human dose based on body surface area comparisons for 28 days prior to mating and to female rats for 15 days prior to mating through day seven of gestation. There was, however, an alteration of the estrous cycle in female rats.

13.2 Animal Toxicology and/or Pharmacology

Tenofovir and tenofovir disoproxil fumarate administered in toxicology studies to rats, dogs and monkeys at exposures (based on AUCs) greater than or equal to 6-fold those observed in humans caused bone toxicity. In monkeys the bone toxicity was diagnosed as osteomalacia. Osteomalacia observed in monkeys appeared to be reversible upon dose reduction or discontinuation of tenofovir. In rats and dogs, the bone toxicity manifested as reduced bone mineral density. The mechanism(s) underlying bone toxicity is unknown.

Evidence of renal toxicity was noted in 4 animal species. Increases in serum creatinine, BUN, glycosuria, proteinuria, phosphaturia, and/or calciuria and decreases in serum phosphate were observed to varying degrees in these animals. These toxicities were noted at exposures (based on AUCs) 2–20 times higher than those observed in humans. The relationship of the renal abnormalities, particularly the phosphaturia, to the bone toxicity is not known.

14 CLINICAL STUDIES

Clinical Study 934 supports the use of TRUVADA tablets for the treatment of HIV-1 infection. Additional data in support of the use of TRUVADA are derived from Study 903, in which lamivudine and tenofovir disoproxil fumarate (tenofovir DF) were used in combination in treatment-naive adults, and clinical Study 303 in which emtricitabine and lamivudine demonstrated comparable efficacy, safety and resistance patterns as part of multidrug regimens. For additional information about these trials, please consult the prescribing information for tenofovir DF and emtricitabine.

14.1 Study 934

Data through 144 weeks are reported for Study 934, a randomized, open-label, active-controlled multicenter trial comparing emtricitabine + tenofovir DF administered in combination with efavirenz versus zidovudine/lamivudine fixed-dose combination administered in combination with efavirenz in 511 antiretroviral-naive subjects. From Weeks 96 to 144 of the trial, subjects received TRUVADA with efavirenz in place of emtricitabine + tenofovir DF with efavirenz. Subjects had a mean age of 38 years (range 18–80), 86% were male, 59% were Caucasian and 23% were Black. The mean baseline CD4^+ cell count was 245 cells/mm^3 (range 2–1191) and median baseline plasma HIV-1 RNA was 5.01 log10 copies/mL (range 3.56–6.54). Subjects were stratified by baseline CD4^+ cell count (< or ≥200 cells/mm^3); 41% had CD4^+ cell counts <200 cells/mm^3 and 51% of subjects had baseline viral loads >100,000 copies/mL. Treatment outcomes through 48 and 144 weeks for those subjects who did not have efavirenz resistance at baseline are presented in Table 10.

Table 10 Outcomes of Randomized Treatment at Week 48 and 144 (Study 934)
Outcomes | At Week 48 |  | At Week 144
Outcomes | FTC + TDF + EFV (N=244) | AZT/3TC + EFV (N=243) | FTC + TDF + EFV (N=227) [Subjects who were responders at Week 48 or Week 96 (HIV-1 RNA <400 copies/mL) but did not consent to continue trial after Week 48 or Week 96 were excluded from analysis.] | AZT/3TC + EFV (N=229)
Responder [Subjects achieved and maintained confirmed HIV-1 RNA <400 copies/mL through Weeks 48 and 144.] | 84% | 73% | 71% | 58%
Virologic failure [Includes confirmed viral rebound and failure to achieve confirmed <400 copies/mL through Weeks 48 and 144.] | 2% | 4% | 3% | 6%
Rebound | 1% | 3% | 2% | 5%
Never suppressed | 0% | 0% | 0% | 0%
Change in antiretroviral regimen | 1% | 1% | 1% | 1%
Death | <1% | 1% | 1% | 1%
Discontinued due to adverse event | 4% | 9% | 5% | 12%
Discontinued for other reasons [Includes lost to follow-up, subject withdrawal, noncompliance, protocol violation and other reasons.] | 10% | 14% | 20% | 22%

Through Week 48, 84% and 73% of subjects in the emtricitabine + tenofovir DF group and the zidovudine/lamivudine group, respectively, achieved and maintained HIV-1 RNA <400 copies/mL (71% and 58% through Week 144). The difference in the proportion of subjects who achieved and maintained HIV-1 RNA <400 copies/mL through 48 weeks largely results from the higher number of discontinuations due to adverse events and other reasons in the zidovudine/lamivudine group in this open-label trial. In addition, 80% and 70% of subjects in the emtricitabine + tenofovir DF group and the zidovudine/lamivudine group, respectively, achieved and maintained HIV-1 RNA <50 copies/mL through Week 48 (64% and 56% through Week 144). The mean increase from baseline in CD4^+ cell count was 190 cells/mm^3 in the emtricitabine + tenofovir DF group and 158 cells/mm^3 in the zidovudine/lamivudine group at Week 48 (312 and 271 cells/mm^3 at Week 144).

Through 48 weeks, 7 subjects in the emtricitabine + tenofovir DF group and 5 subjects in the zidovudine/lamivudine group experienced a new CDC Class C event (10 and 6 subjects through 144 weeks).

16 HOW SUPPLIED/STORAGE AND HANDLING

The blue, capsule-shaped, film-coated, tablets contain 200 mg of emtricitabine and 300 mg of tenofovir disoproxil fumarate (which is equivalent to 245 mg of tenofovir disoproxil), are debossed with "GILEAD" on one side and with "701" on the other side, and are available in unit of use bottles (containing a dessicant [silica gel canister or sachet] and closed with a child-resistant closure) of:

- 30 tablets (NDC 61958-0701-1)

STORAGE AND HANDLING

Store at 25 °C (77 °F), excursions permitted to 15–30 °C (59–86 °F) (see USP Controlled Room Temperature).

- Keep container tightly closed
- Dispense only in original container
- Do not use if seal over bottle opening is broken or missing.

17 PATIENT COUNSELING INFORMATION and FDA-APPROVED PATIENT LABELING

Information for Patients

Patients should be advised that:

- TRUVADA is not a cure for HIV-1 infection and patients may continue to experience illnesses associated with HIV-1 infection, including opportunistic infections. Patients should remain under the care of a physician when using TRUVADA.
- The use of TRUVADA has not been shown to reduce the risk of transmission of HIV-1 to others through sexual contact or blood contamination. Patients should be advised to continue to practice safer sex and to use latex or polyurethane condoms to lower the chance of sexual contact with any body fluids such as semen, vaginal secretions or blood. Patients should be advised never to re-use or share needles.
- The long term effects of TRUVADA are unknown.
- TRUVADA tablets are for oral ingestion only.
- It is important to take TRUVADA with combination therapy on a regular dosing schedule to avoid missing doses.
- Lactic acidosis and severe hepatomegaly with steatosis, including fatal cases, have been reported. Treatment with TRUVADA should be suspended in any patients who develop clinical symptoms suggestive of lactic acidosis or pronounced hepatotoxicity (including nausea, vomiting, unusual or unexpected stomach discomfort, and weakness) [See Warnings and Precautions (5.1)].
- All patients with HIV-1 should be tested for hepatitis B virus (HBV) before initiating antiretroviral therapy.
- Severe acute exacerbations of hepatitis B have been reported in patients who are coinfected with HBV and HIV-1 and have discontinued TRUVADA.
- Renal impairment, including cases of acute renal failure and Fanconi syndrome, has been reported in association with the use of VIREAD. TRUVADA should be avoided with concurrent or recent use of a nephrotoxic agent [See Warnings and Precautions (5.3)]. Dosing interval of TRUVADA may need adjustment in patients with renal impairment [See Dosage and Administration (2.2)].
- TRUVADA should not be coadministered with ATRIPLA, EMTRIVA, or VIREAD; or with drugs containing lamivudine, including Combivir (lamivudine/zidovudine), Epivir or Epivir-HBV (lamivudine), Epzicom (abacavir sulfate/lamivudine), or Trizivir (abacavir sulfate/lamivudine/zidovudine) [See Warnings and Precautions (5.4)].
- TRUVADA should not be administered with HEPSERA [See Warnings and Precautions (5.4)].
- Decreases in bone mineral density have been observed with the use of VIREAD. Bone monitoring should be considered in patients who have a history of pathologic bone fracture or at risk for osteopenia [See Warnings and Precautions (5.5)].

FDA-Approved Patient Labeling

TRUVADA® (tru-VAH-dah) tablets

Generic name: emtricitabine and tenofovir disoproxil fumarate
(em tri SIT uh bean and te NOE' fo veer dye soe PROX il FYOU mar ate)

Read the Patient Information that comes with TRUVADA before you start taking it and each time you get a refill. There may be new information. This information does not take the place of talking to your healthcare provider about your medical condition or treatment. You should stay under a healthcare provider's care when taking TRUVADA. Do not change or stop your medicine without first talking with your healthcare provider. Talk to your healthcare provider or pharmacist if you have any questions about TRUVADA.

What is the most important information I should know about TRUVADA?

- Some people who have taken medicine like TRUVADA (nucleoside analogs) have developed a serious condition called lactic acidosis (build up of an acid in the blood). Lactic acidosis can be a medical emergency and may need to be treated in the hospital. Call your healthcare provider right away if you get the following signs or symptoms of lactic acidosis.
  - You feel very weak or tired.
  - You have unusual (not normal) muscle pain.
  - You have trouble breathing.
  - You have stomach pain with nausea and vomiting.
  - You feel cold, especially in your arms and legs.
  - You feel dizzy or lightheaded.
  - You have a fast or irregular heartbeat.
- Some people who have taken medicines like TRUVADA have developed serious liver problems called hepatotoxicity, with liver enlargement (hepatomegaly) and fat in the liver (steatosis). Call your healthcare provider right away if you get the following signs or symptoms of liver problems.
  - Your skin or the white part of your eyes turns yellow (jaundice).
  - Your urine turns dark.
  - Your bowel movements (stools) turn light in color.
  - You don't feel like eating food for several days or longer.
  - You feel sick to your stomach (nausea).
  - You have lower stomach area (abdominal) pain.
- You may be more likely to get lactic acidosis or liver problems if you are female, very overweight (obese), or have been taking nucleoside analog medicines, like TRUVADA, for a long time.
- If you are also infected with the hepatitis B virus (HBV), you need close medical follow-up for several months after stopping treatment with TRUVADA. Follow-up includes medical exams and blood tests to check for HBV that could be getting worse. Patients with hepatitis B virus infection, who take TRUVADA and then stop it, may get "flare-ups" of their hepatitis. A "flare-up" is when the disease suddenly returns in a worse way than before.

What is TRUVADA?

TRUVADA is a type of medicine called an HIV-1 (human immunodeficiency virus) nucleoside analog reverse transcriptase inhibitor (NRTI). TRUVADA contains 2 medicines, EMTRIVA® (emtricitabine) and VIREAD® (tenofovir disoproxil fumarate, or tenofovir DF) combined in one pill. TRUVADA is always used with other anti-HIV-1 medicines to treat people with HIV-1 infection. TRUVADA is for adults and pediatric patients 12 years of age and older. TRUVADA has not been studied in children under age 12 or weighing less than 35 kg (77 lb) or in adults over age 65.

HIV infection destroys CD4^+ T cells, which are important to the immune system. The immune system helps fight infection. After a large number of T cells are destroyed, acquired immune deficiency syndrome (AIDS) develops.

TRUVADA helps block HIV-1 reverse transcriptase, a chemical in your body (enzyme) that is needed for HIV-1 to multiply. TRUVADA lowers the amount of HIV-1 in the blood (viral load). TRUVADA may also help to increase the number of T cells (CD4^+ cells). Lowering the amount of HIV-1 in the blood lowers the chance of death or infections that happen when your immune system is weak (opportunistic infections).

TRUVADA does not cure HIV-1 infection or AIDS. The long-term effects of TRUVADA are not known at this time. People taking TRUVADA may still get opportunistic infections or other conditions that happen with HIV-1 infection. Opportunistic infections are infections that develop because the immune system is weak. Some of these conditions are pneumonia, herpes virus infections, and Mycobacterium avium complex (MAC) infection. It is very important that you see your healthcare provider regularly while taking TRUVADA.

TRUVADA does not lower your chance of passing HIV-1 to other people through sexual contact, sharing needles, or being exposed to your blood. For your health and the health of others, it is important to always practice safer sex by using a latex or polyurethane condom or other barrier to lower the chance of sexual contact with semen, vaginal secretions, or blood. Never use or share dirty needles.

Who should not take TRUVADA?

- Do not take TRUVADA if you are allergic to TRUVADA or any of its ingredients. The active ingredients of TRUVADA are emtricitabine and tenofovir DF. See the end of this leaflet for a complete list of ingredients.
- Do not take TRUVADA if you are already taking ATRIPLA®, Combivir (lamivudine/zidovudine), EMTRIVA, Epivir or Epivir-HBV (lamivudine), Epzicom (abacavir sulfate/lamivudine), Trizivir (abacavir sulfate/lamivudine/zidovudine), or VIREAD because these medicines contain the same or similar active ingredients.
- Do not take TRUVADA to treat your HIV infection if you are also taking HEPSERA® to treat your HBV infection.

What should I tell my healthcare provider before taking TRUVADA?

Tell your healthcare provider if you:

- are pregnant or planning to become pregnant. We do not know if TRUVADA can harm your unborn child. You and your healthcare provider will need to decide if TRUVADA is right for you. If you use TRUVADA while you are pregnant, talk to your healthcare provider about how you can be on the TRUVADA Antiviral Pregnancy Registry.
- are breast-feeding. You should not breast feed if you are HIV-positive because of the chance of passing the HIV virus to your baby. Also, it is not known if TRUVADA can pass into your breast milk and if it can harm your baby. If you are a woman who has or will have a baby, talk with your healthcare provider about the best way to feed your baby.
- have kidney problems or are undergoing kidney dialysis treatment.
- have bone problems.
- have liver problems including hepatitis B virus infection.

Tell your healthcare provider about all the medicines you take, including prescription and non-prescription medicines, vitamins, and herbal supplements. Especially tell your healthcare provider if you take:

- Videx, Videx EC (didanosine). Tenofovir DF (a component of TRUVADA) may increase the amount of Videx in your blood. You may need to be followed more carefully if you are taking TRUVADA and Videx together. Also, the dose of didanosine may need to be reduced.
- Reyataz (atazanavir sulfate) or Kaletra (lopinavir/ritonavir). These medicines may increase the amount of tenofovir DF (a component of TRUVADA) in your blood, which could result in more side effects. You may need to be followed more carefully if you are taking TRUVADA and Reyataz or Kaletra together. TRUVADA may decrease the amount of Reyataz in your blood. If you are taking TRUVADA and Reyataz together, you should also be taking Norvir (ritonavir).

Keep a complete list of all the medicines that you take. Make a new list when medicines are added or stopped. Give copies of this list to all of your healthcare providers and pharmacist every time you visit your healthcare provider or fill a prescription.

How should I take TRUVADA?

- Take TRUVADA exactly as your healthcare provider prescribed it. Follow the directions from your healthcare provider, exactly as written on the label.
- The usual dose of TRUVADA is 1 tablet once a day. TRUVADA is always used with other anti-HIV-1 medicines. If you have kidney problems, you may need to take TRUVADA less often.
- TRUVADA may be taken with or without a meal. Food does not affect how TRUVADA works. Take TRUVADA at the same time each day.
- If you forget to take TRUVADA, take it as soon as you remember that day. Do not take more than 1 dose of TRUVADA in a day. Do not take 2 doses at the same time. Call your healthcare provider or pharmacist if you are not sure what to do. It is important that you do not miss any doses of TRUVADA or your anti-HIV-1 medicines.
- When your TRUVADA supply starts to run low, get more from your healthcare provider or pharmacy. This is very important because the amount of virus in your blood may increase if the medicine is stopped for even a short time. The virus may develop resistance to TRUVADA and become harder to treat.
- Do not change your dose or stop taking TRUVADA without first talking with your healthcare provider. Stay under a healthcare provider's care when taking TRUVADA.
- If you take too much TRUVADA, call your local poison control center or emergency room right away.

What should I avoid while taking TRUVADA?

- Do not breast-feed. See "What should I tell my healthcare provider before taking TRUVADA?"
- Avoid doing things that can spread HIV infection since TRUVADA does not stop you from passing the HIV infection to others.
  - Do not share needles or other injection equipment.
  - Do not share personal items that can have blood or body fluids on them, like toothbrushes or razor blades.
  - Do not have any kind of sex without protection. Always practice safer sex by using a latex or polyurethane condom or other barrier to reduce the chance of sexual contact with semen, vaginal secretions, or blood.
- ATRIPLA, Combivir (lamivudine/zidovudine), EMTRIVA, Epivir or Epivir-HBV (lamivudine), Epzicom (abacavir sulfate/lamivudine), Trizivir (abacavir sulfate/lamivudine/zidovudine), or VIREAD.
  TRUVADA should not be used with these medicines.
- TRUVADA should not be used with HEPSERA.

What are the possible side effects of TRUVADA?

TRUVADA may cause the following serious side effects (see "What is the most important information I should know about TRUVADA?"):

- Lactic acidosis (buildup of an acid in the blood). Lactic acidosis can be a medical emergency and may need to be treated in the hospital. Call your doctor right away if you get signs of lactic acidosis. (See "What is the most important information I should know about TRUVADA?")
- Serious liver problems (hepatotoxicity), with liver enlargement (hepatomegaly) and fat in the liver (steatosis). Call your healthcare provider right away if you get any signs of liver problems. (See "What is the most important information I should know about TRUVADA?")
- "Flare-ups" of hepatitis B virus infection, in which the disease suddenly returns in a worse way than before, can occur if you stop taking TRUVADA. Your healthcare provider will monitor your condition for several months after stopping TRUVADA if you have both HIV-1 and HBV infection. TRUVADA is not approved for the treatment of hepatitis B virus infection. If you have advanced liver disease and stop treatment with TRUVADA, the "flare-up" of hepatitis B may cause your liver function to decline.
- Kidney problems. If you have had kidney problems in the past or take other medicines that can cause kidney problems, your healthcare provider should do regular blood tests to check your kidneys.
- Changes in bone mineral density (thinning bones). Laboratory tests show changes in the bones of patients treated with VIREAD, a component of TRUVADA. Some HIV patients treated with VIREAD developed thinning of the bones (osteopenia) which could lead to fractures. If you have had bone problems in the past, your healthcare provider may need to do tests to check your bone mineral density or may prescribe medicines to help your bone mineral density. Additionally, bone pain and softening of the bone (which may contribute to fractures) may occur as a consequence of kidney problems.

Other side effects with TRUVADA when used with other anti-HIV-1 medicines include:

- Changes in body fat have been seen in some patients taking TRUVADA and other anti-HIV-1 medicines. These changes may include increased amount of fat in the upper back and neck ("buffalo hump"), breast, and around the main part of your body (trunk). Loss of fat from the legs, arms and face may also happen. The cause and long term health effect of these conditions are not known at this time.
- In some patients with advanced HIV infection (AIDS), signs and symptoms of inflammation from previous infections may occur soon after anti-HIV treatment is started. It is believed that these symptoms are due to an improvement in the body's immune response, enabling the body to fight infections that may have been present with no obvious symptoms. If you notice any symptoms of infection, please inform your doctor immediately.

The most common side effects of EMTRIVA or VIREAD when used with other anti-HIV-1 medicines are: diarrhea, dizziness, nausea, headache, fatigue, abnormal dreams, sleeping problems, rash, depression, and vomiting. Additional side effects are lactic acidosis, kidney problems (including decline or failure of kidney function), inflammation of the pancreas, inflammation of the liver, allergic reaction (including swelling of the face, lips, tongue, or throat), shortness of breath, pain, fatty liver, stomach pain, weakness, indigestion, intestinal gas, and high volume of urine and thirst caused by kidney problems. Muscle pain and muscle weakness, bone pain, and softening of the bone (which may contribute to fractures) as a consequence of kidney problems have been reported. Skin discoloration (small spots or freckles) may also happen with TRUVADA.

These are not all the side effects of TRUVADA. If you have questions about side effects, ask your healthcare provider. Report any new or continuing symptoms to your healthcare provider right away. Your healthcare provider may be able to help you manage these side effects.

How do I store TRUVADA?

- Keep TRUVADA and all other medicines out of reach of children.
- Store TRUVADA at room temperature 77 °F (25 °C).
- Keep TRUVADA in its original container and keep the container tightly closed.
- Do not keep medicine that is out of date or that you no longer need. If you throw any medicines away make sure that children will not find them.

General information about TRUVADA:

Medicines are sometimes prescribed for conditions that are not mentioned in patient information leaflets. Do not use TRUVADA for a condition for which it was not prescribed. Do not give TRUVADA to other people, even if they have the same symptoms you have. It may harm them.

This leaflet summarizes the most important information about TRUVADA. If you would like more information, talk with your healthcare provider. You can ask your healthcare provider or pharmacist for information about TRUVADA that is written for health professionals. For more information, you may also call 1-800-GILEAD-5 or access the TRUVADA website at www.TRUVADA.com.

Do not use TRUVADA if seal over bottle opening is broken or missing.

What are the ingredients of TRUVADA?

Active Ingredients: emtricitabine and tenofovir disoproxil fumarate

Inactive Ingredients: Croscarmellose sodium, lactose monohydrate, magnesium stearate, microcrystalline cellulose, and pregelatinized starch (gluten free). The tablets are coated with Opadry II Blue Y-30-10701 containing FD&C Blue #2 aluminum lake, hydroxypropyl methylcellulose 2910, lactose monohydrate, titanium dioxide, and triacetin.

Rx Only

July 2011

TRUVADA, EMTRIVA, HEPSERA and VIREAD are registered trademarks of Gilead Sciences, Inc. ATRIPLA is a trademark of Bristol-Myers Squibb & Gilead Sciences, LLC. All other trademarks referenced herein are the property of their respective owners.

21-752-GS-024

PRINCIPAL DISPLAY PANEL - Representative Bottle Label

NDC 61958-0701-1

Truvada®
(emtricitabine and tenofovir
disoproxil fumarate)
Tablets

30 tablets

Rx only

Repacked by:
H.J. Harkins Company, Inc.
Nipomo, CA 93444